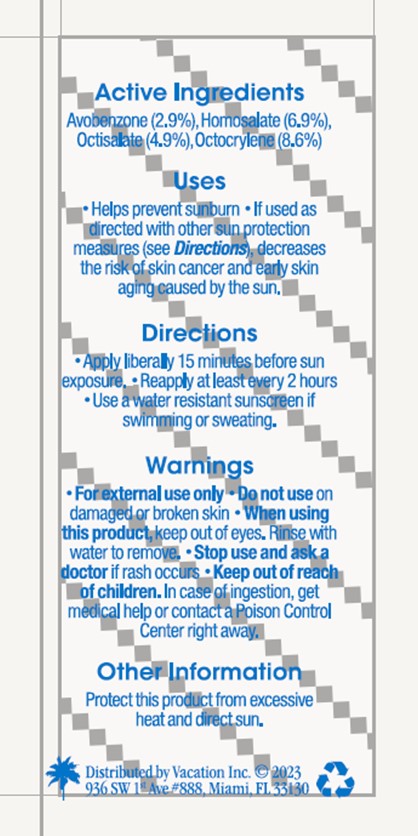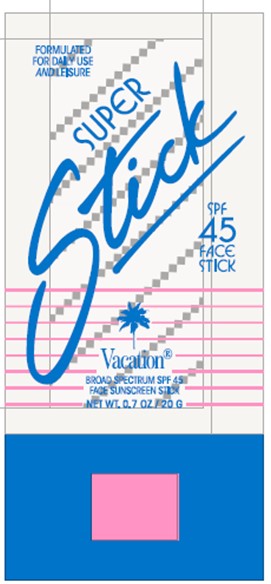 DRUG LABEL: Vacation Super
NDC: 80641-017 | Form: STICK
Manufacturer: Vacation Inc.
Category: otc | Type: HUMAN OTC DRUG LABEL
Date: 20240312

ACTIVE INGREDIENTS: OCTOCRYLENE 8.6 g/100 g; AVOBENZONE 2.9 g/100 g; HOMOSALATE 6.9 g/100 g; OCTISALATE 4.9 g/100 g
INACTIVE INGREDIENTS: WATER

Vacation Super Stick SPF 45

DOSAGE AND ADMINISTRATION

Apply liberally 15 minutes before sun exposure

Reapply at least every 2 hours

WARNINGS

For external use only

Do not use on damaged or broken skin

When using this product keep out of eyes

Rinse with water to remove

Stop use and ask a doctor if rash occurs

Inactives

Aloe Barbadensis Leaf Juice

Butyloctyl Salicylate

Calcium Sodium Phosphosilicate

Camellia Sinensis Leaf Extract

Caprylic/Capric Triglyceride

Ceramide NG

Ceramide NP

Cetyl Esters

Chlorella Vulgaris Extract

Cocos Nucifera (Coconut) Extract

Ethylhexylglycerin

Fragrance

Glycerin

Hyaluronic Acid

Lauroyl Lysine

Methylheptylglycerin

Musa Sapientum (Banana) Fruit Extract

Niacinamide

Olea Europaea (Olive) Fruit Oil

Polyglyceryl-10 Caprylate/Caprate

Polyurethane-35

Ricinus Communis (Castor) Seed Oil

Saccharomyces Ferment

Sodium Phytate

Sodium Stearate

Sorbitan Olivate

Tapioca Starch

Tocopherol

Tridecane

Trimethylpentanediol/Adipic Acid/Glycerin Crosspolymer

Undecane

Water

Indications and Usage

Helps prevent sunburn

If used as directed with other sun protection measures (see Directions), decreases the risk of skin cancer and early skin aging caused by the sun

Keep out of reach of children

In case of ingestion, get medical help or contact a Poison Control Center right away

Purpose

Sunscreen